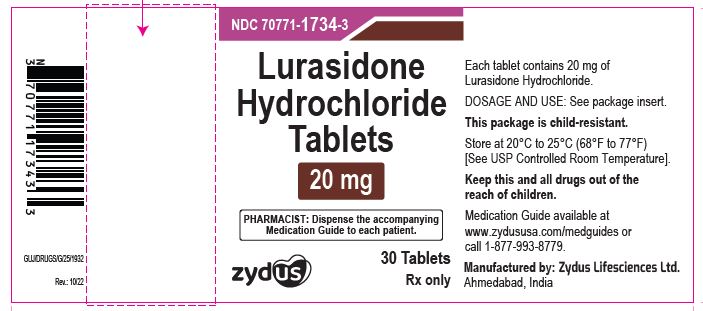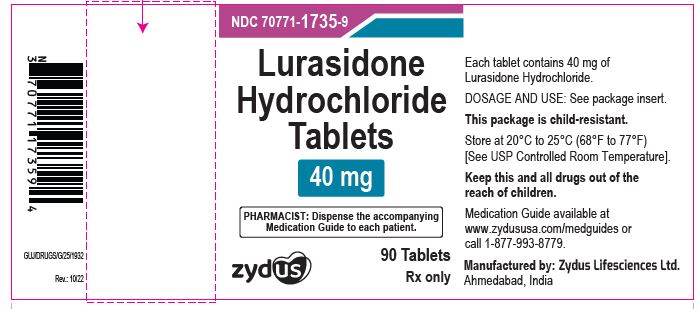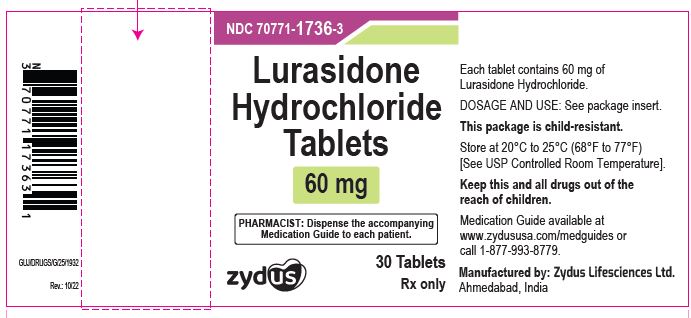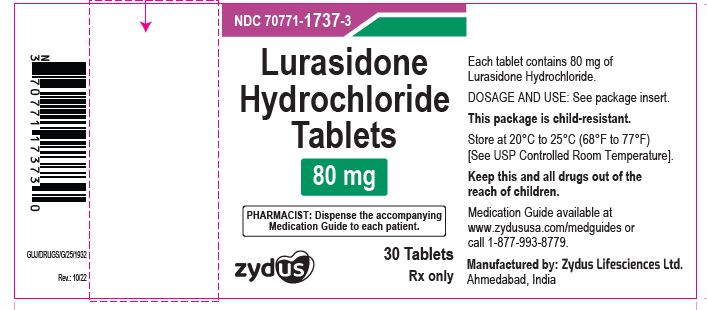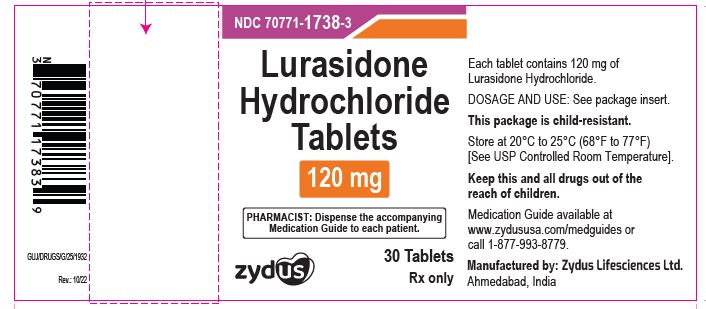 DRUG LABEL: Lurasidone hydrochloride
NDC: 70771-1734 | Form: TABLET, COATED
Manufacturer: Zydus Lifesciences Limited
Category: prescription | Type: HUMAN PRESCRIPTION DRUG LABEL
Date: 20241130

ACTIVE INGREDIENTS: LURASIDONE HYDROCHLORIDE 20 mg/1 1
INACTIVE INGREDIENTS: CELLULOSE, MICROCRYSTALLINE; CITRIC ACID MONOHYDRATE; CROSCARMELLOSE SODIUM; FERRIC OXIDE YELLOW; HYPROMELLOSES; LACTOSE MONOHYDRATE; MAGNESIUM STEARATE; POLOXAMER 407; POLYETHYLENE GLYCOL, UNSPECIFIED; POLYVINYL ALCOHOL, UNSPECIFIED; STARCH, CORN; TALC; TITANIUM DIOXIDE

Lurasidone Hydrochloride Tablets

PACKAGE LABEL.PRINCIPAL DISPLAY PANEL

NDC 70771-1734-3

Lurasidone hydrochloride tablets, 20 mg

30 tablets

Rx only

NDC 70771-1735-9

Lurasidone hydrochloride tablets, 40 mg

90 tablets

Rx only

NDC 70771-1736-3

Lurasidone hydrochloride tablets, 60 mg

30 tablets

Rx only

NDC 70771-1737-3

Lurasidone hydrochloride tablets, 80 mg

30 tablets

Rx only

NDC 70771-1738-3

Lurasidone hydrochloride tablets, 120 mg

30 tablets

Rx only